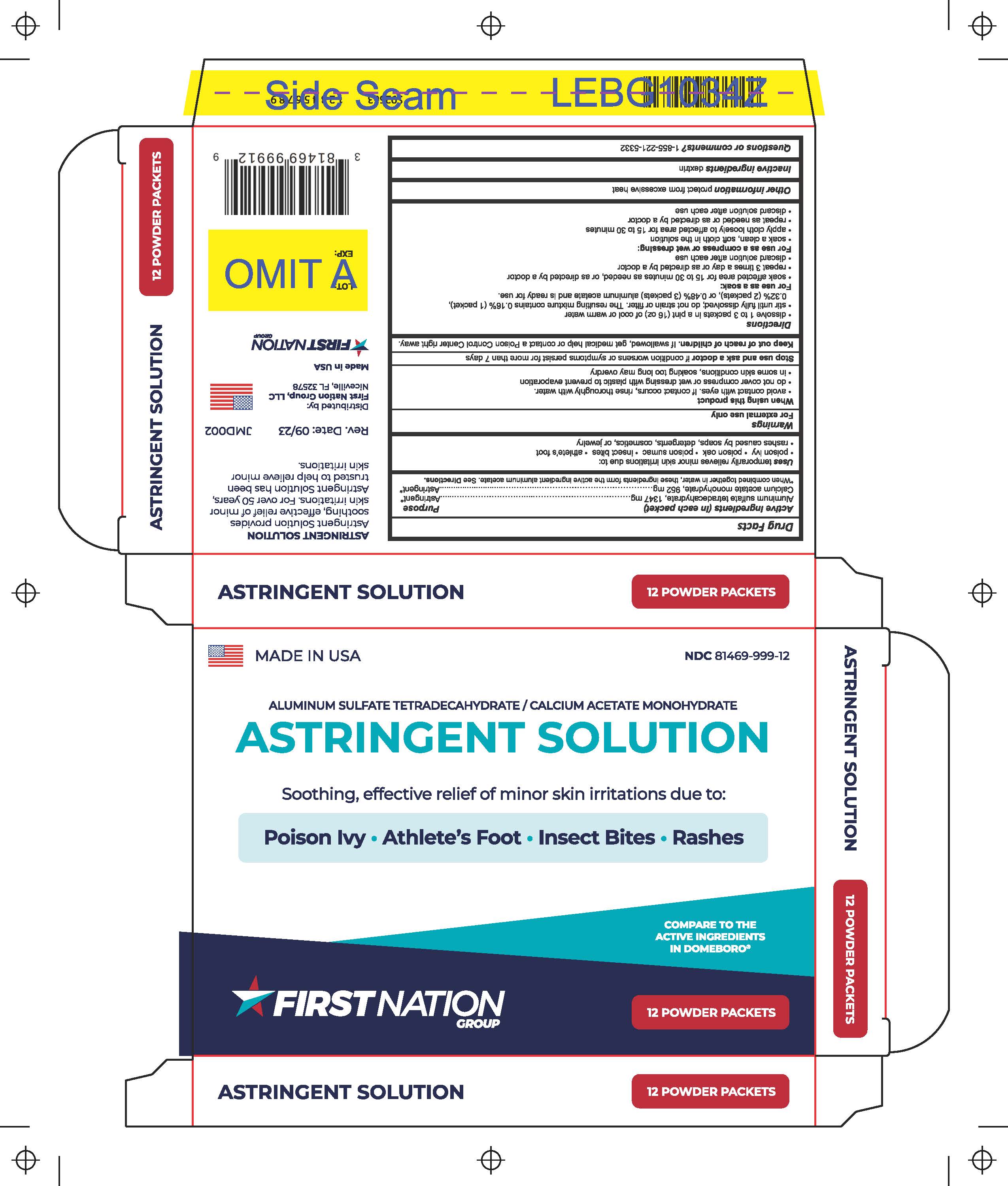 DRUG LABEL: Astringent Solution
NDC: 81469-999 | Form: POWDER, FOR SOLUTION
Manufacturer: First Nation Group
Category: otc | Type: HUMAN OTC DRUG LABEL
Date: 20250707

ACTIVE INGREDIENTS: CALCIUM ACETATE MONOHYDRATE 952 mg/2299 mg; ALUMINUM SULFATE TETRADECAHYDRATE 1347 mg/2299 mg
INACTIVE INGREDIENTS: ICODEXTRIN

Active Ingredients (in each packet) Purpose

Aluminum sulfate tetradecahydrate, 1347 mg Astringent*
Calcium acetate monohydrate, 952 mg Astringent*

*When combined together in water, these ingredients form the
active ingredient aluminum acetate. See Directions.

Uses

Temporarily relieves minor skin irritations due to:

- Poison ivy
- Poison oak
- Poison sumac
- Insect bites
- Athlete's foot
- Rashes caused by soaps, detergents, cosmetics, or jewelry

PURPOSE

Temporarily relieves minor skin irritations due to:

- Poison ivy
- Poison oak
- Poison sumac
- Insect bites
- Athlete's foot
- Rashes caused by soaps, detergents, cosmetics, or jewelry

WARNINGS

FOR EXTERNAL USE ONLY

When using this product

- Avoid contact with eyes. If contact occurs, rinse thoroughly with water.
- Do not cover compress or wet dressing with plastic to prevent evaporation.
- In some skin conditions, soaking too long may overdry.

Stop use and ask a doctor if condition worsens or symptoms persist for more than 7 days.

Keep out of reach of children. If swallowed, get medical help or contact a Poison Control Center right away.

Directions

- Dissolve 1 to 3 packets in a pint (16 oz) of cool or warm water.
- Stir until fully dissolved; do not strain or filter. The resulting mixture contains 0.16% (1 packet), 0.32% (2 packets), or 0.48% (3packets) aluminum acetate and is ready for use.

For use as a soak:

- Soak affected area for 15 to 30 minutes as needed, or as directed by a doctor.
- Repeat 3 times a day or as directed by a doctor.
- Discard solution after each use.

For use as a compress or wet dressing:

- Soak a clean, soft cloth in the solution.
- Apply cloth loosely to affected area for 15 to 30 minutes.
- Repeat as needed or as directed by a doctor.
- Discard solution after each use.

STORAGE AND HANDLING

Protect from excessive heat.

INACTIVE INGREDIENT

Dextrin

QUESTIONS

1-855-221-5332

Distributed by:

First Nation Group, LLC

Niceville, FL 32578